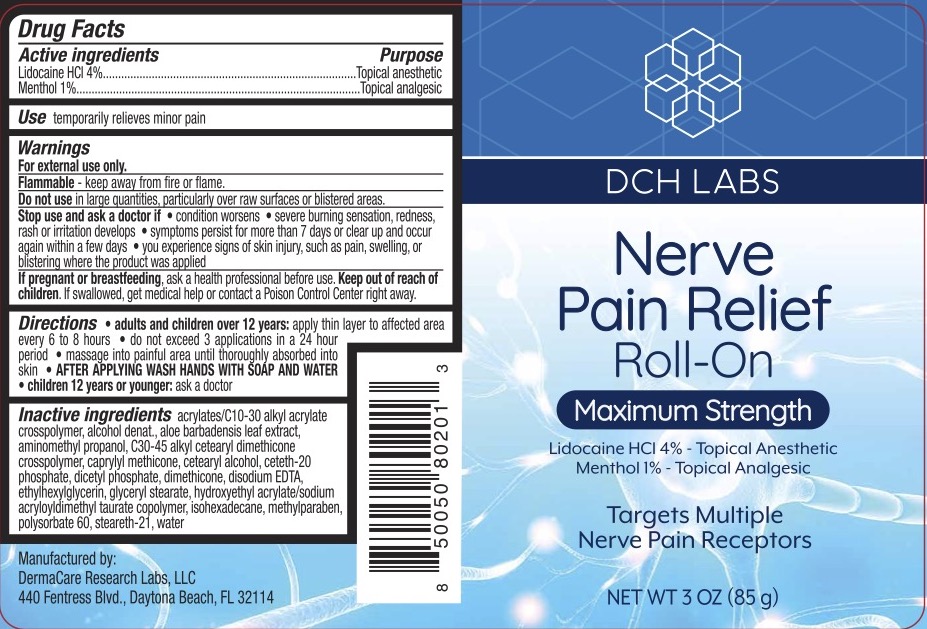 DRUG LABEL: DCH Nerve Pain Relief Roll-On
NDC: 72839-014 | Form: GEL
Manufacturer: Derma Care Research Labs, LLC
Category: otc | Type: HUMAN OTC DRUG LABEL
Date: 20241219

ACTIVE INGREDIENTS: MENTHOL 1 g/100 g; LIDOCAINE HYDROCHLORIDE 4 g/100 g
INACTIVE INGREDIENTS: ISOHEXADECANE; CETETH-20 PHOSPHATE; HYDROXYETHYL ACRYLATE/SODIUM ACRYLOYLDIMETHYL TAURATE COPOLYMER (45000 MPA.S AT 1%); STEARETH-21; ETHYLHEXYLGLYCERIN; GLYCERYL MONOSTEARATE; CARBOMER COPOLYMER TYPE B (ALLYL PENTAERYTHRITOL CROSSLINKED); ALOE VERA LEAF; AMINOMETHYLPROPANOL; DIHEXADECYL PHOSPHATE; EDETATE DISODIUM; CAPRYLYL TRISILOXANE; METHYLPARABEN; CETOSTEARYL ALCOHOL; WATER; ALCOHOL; C30-45 ALKYL CETEARYL DIMETHICONE CROSSPOLYMER; DIMETHICONE 200

DCH Nerve Pain Relief Roll-On

ACTIVE INGREDIENT

Lidocaine HCl 4%, Menthol 1%

PURPOSE

Topical Analgesic

DOSAGE AND ADMINISTRATION

Temporarily relieves minor pain.

WARNINGS

For external use only. Flammable--keep away from fire or flame. Do not use in large quantities, particularly over raw surfaces or blistered areas.

Stop use and ask a doctor if the condition worsens, symptoms persist for more than 7 days or clear up and occur again within a few days, you experience signs of skin injury, such as pain, swelling, or blistering where the product was applied.

KEEP OUT OF REACH OF CHILDREN

In case of accidental ingestion, seek professional assistance or contact a Poison Control Center immediately.

INDICATIONS AND USAGE

Adults and children 12 years and older: apply to the affected area, not more than 6 to 8 hours. Do not exceed 3 applications in a 24-hour period. Massage into painful area until thoroughly absorbed into the skin. AFTER APPLYING WASH HANDS WITH SOAP ANDWATER. Children under 12 years of age: ask a doctor.

INACTIVE INGREDIENT

Acrylates/C10-30 Alkyl Acrylate Crosspolymer, Alcohol Denat., Aloe Barbadensis Leaf Extract, Aminomethyl Propanol, C30-45 Alkyl Cetearyl Dimethicone Crosspolymer, Caprylyl Methicone, Cetearyl Alcohol, Ceteth-20 Phosphate, Dicetyl Phosphate, Dimethicone, Disodium EDTA, Ethylhexylglycerin, Glyceryl Stearate, Hydroxyethyl Acrylate/Sodium Acryloyldimethyl Taurate Copolymer, Isohexadecane, Methylparaben, Polysorbate 60, Steareth-21, Water.

PREGNANCY OR BREAST FEEDING

If pregnant or breastfeeding, ask a health professional before use.